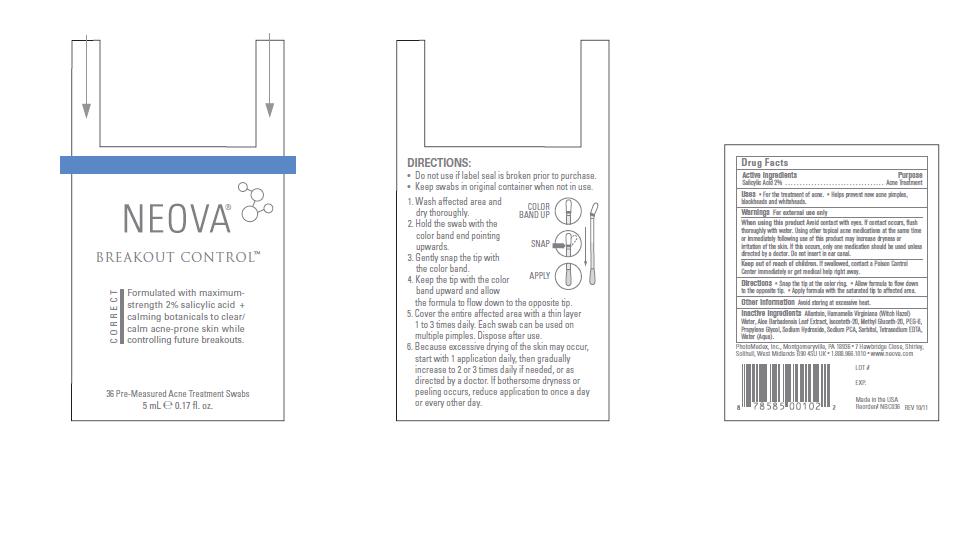 DRUG LABEL: Neova 
NDC: 62362-119 | Form: SWAB
Manufacturer: PhotoMedex, Inc.
Category: otc | Type: HUMAN OTC DRUG LABEL
Date: 20111228

ACTIVE INGREDIENTS: Salicylic Acid 2 mL/100 mL
INACTIVE INGREDIENTS: Allantoin; Hamamelis Virginiana Leaf Water; Aloe Vera Leaf; Isoceteth-20; Methyl Gluceth-20; Polyethylene Glycol 300 ; Propylene Glycol; Sodium Hydroxide; Sodium Pyrrolidone Carboxylate; Sorbitol; Edetate Sodium; Water

Neova Breakout Control - Drug Facts

Active Ingredients

Salicylic Acid 2%

Purpose

Acne Treatment

Uses

• For the treatment of acne. • Helps prevent new acne pimples,
blackheads and whiteheads.

Warnings

For external use only

When using this product

Avoid contact with eyes. If contact occurs, flush
thoroughly with water. Using other topical acne medications at the same time
or immediately following use of this product may increase dryness or
irritation of the skin. If this occurs, only one medication should be used unless
directed by a doctor. Do not insert in ear canal.

Keep out of reach of children.

If swallowed, contact a Poison Control
Center immediately or get medical help right away.

Directions

• Snap the tip at the color ring. • Allow formula to flow down
to the opposite tip. • Apply formula with the saturated tip to affected area.

Other Information

Avoid storing at excessive heat.

Inactive Ingredients

Allantoin, Hamamelis Virginiana (Witch Hazel)
Water, Aloe Barbadensis Leaf Extract, Isoceteth-20, Methyl Gluceth-20, PEG-6,
Propylene Glycol, Sodium Hydroxide, Sodium PCA, Sorbitol, Tetrasodium EDTA,
Water (Aqua).

Image of Box Label

BreakOutControlBoxLabel112611.jpg